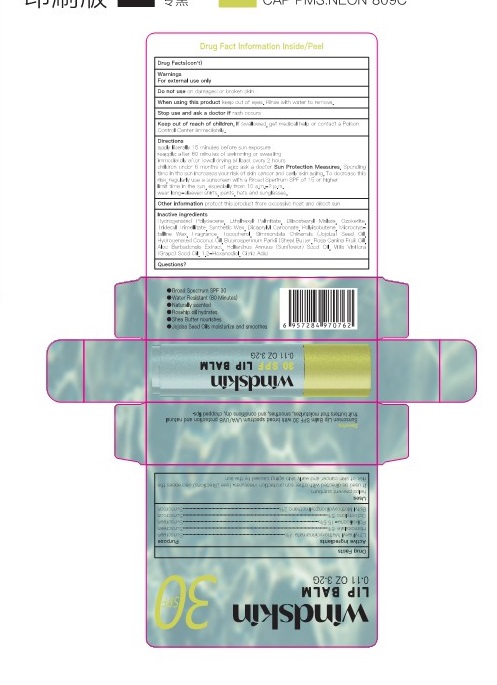 DRUG LABEL: SUNSCREEN LIP BALM
NDC: 84066-101 | Form: LIPSTICK
Manufacturer: Guangzhou Tata Biotechnology Co., Ltd.
Category: otc | Type: HUMAN OTC DRUG LABEL
Date: 20251222

ACTIVE INGREDIENTS: POLYSILICONE-15 5 g/100 g; OCTOCRYLENE 5 g/100 g; OCTINOXATE 7 g/100 g; HOMOSALATE 6 g/100 g; AVOBENZONE 2 g/100 g
INACTIVE INGREDIENTS: SUNFLOWER OIL; POLYISOBUTYLENE (1000 MW); SHEA BUTTER; HYDROGENATED COCONUT OIL; ROSA CANINA FRUIT OIL; ALOE ARBORESCENS LEAF; CERESIN; JOJOBA OIL; DIISOSTEARYL MALATE; DICAPRYLYL CARBONATE; 1,2-HEXANEDIOL; TRIDECYL TRIMELLITATE; PARAFFIN; MICROCRYSTALLINE WAX; GRAPE SEED OIL; CITRIC ACID MONOHYDRATE; ETHYLHEXYL PALMITATE; TOCOPHEROL; HYDROGENATED POLYDECENE (1500 CST) 18.91 g/100 g

SUNSCREEN LIP BALM

Active ingredients
Ethylhexyl Methoxycinnamate 7%
Homosalate 6 %
Polysilicone-15 5%
Octocrylene 5%
Butyl Methoxydibenzoylmethane 2%

PURPOSE

Sunscreen

INACTIVE INGREDIENT

lnactive ingredients：Hydrogenated Polydecene, Ethylhexyl Palmitate, Disostearyl Malate.OzokeriteTridecyl Trimellitate, Synthetic Wax, Dicapryly Carbonate, Polyisobutene, Microcrys-talline Wax，Fragrance, Tocopherol， Simmondsia Chinensis (Jojoba) Seed OilHydrogenated Coconut Oil, Butyrospermum Parkii (Shea) Butter, Rosa Canina Fruit Oi.Aloe Barbadensis Extract, Helianthus Annuus (Sunfower) Seed Oil. Vitis ViniferaGrape) Seed Oil，12-Hexanediol, Citric Acid

Questions or comments?

+1-973-907-6739

INDICATIONS AND USAGE

helps prevent sumburn
if used as directed with other sun protection measures, (see Directions) decreases therisk of skin cancer and early skin aging caused by the sun

WARNINGS

For external use only

Do not use on damaged or broken skin

When using this product keep out of eyes. Rinse with water to remove.

Stop use and ask a doctor if rash occurs

Keep out of reach of children. lf swallowed, get medical help or contact a Poison
Control Center immediately.

Directions
apply liberally 15 minutes before sun exposure
reapply: after 80 minutes of swimming or sweating
immediately after towel drying at least every 2 hours
children under 6 months of age: ask a doctor Sun Protection Measures. Spendingtime in the sun increases your risk of skin cancer and early skin aging. To decrease thisrisk, regularly use a sunscreen with a Broad Spertrum SPF of 15 or higher
limit time in the sun, especially from 10 a.m.-2 p.m.
wear long-sleeved shirts,pants,hats and sunglasses

Other information protect this product from excessive heat and direct sun